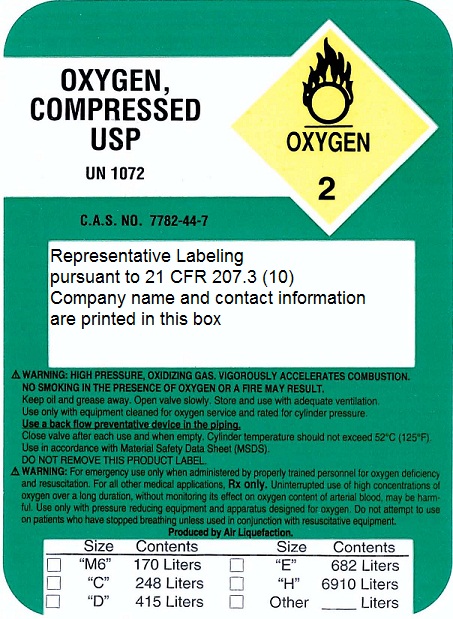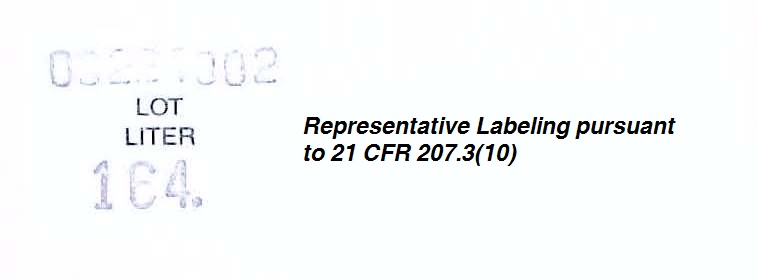 DRUG LABEL: Oxygen
NDC: 66803-001 | Form: GAS
Manufacturer: Georgia Oxygen & Home Health
Category: prescription | Type: HUMAN PRESCRIPTION DRUG LABEL
Date: 20101005

ACTIVE INGREDIENTS: Oxygen 99 L/100 L

Oxygen

Principal for Oxygen Product

Representative Labeling
High Pressure Cylinder Drug Product Label
Lot Sticker